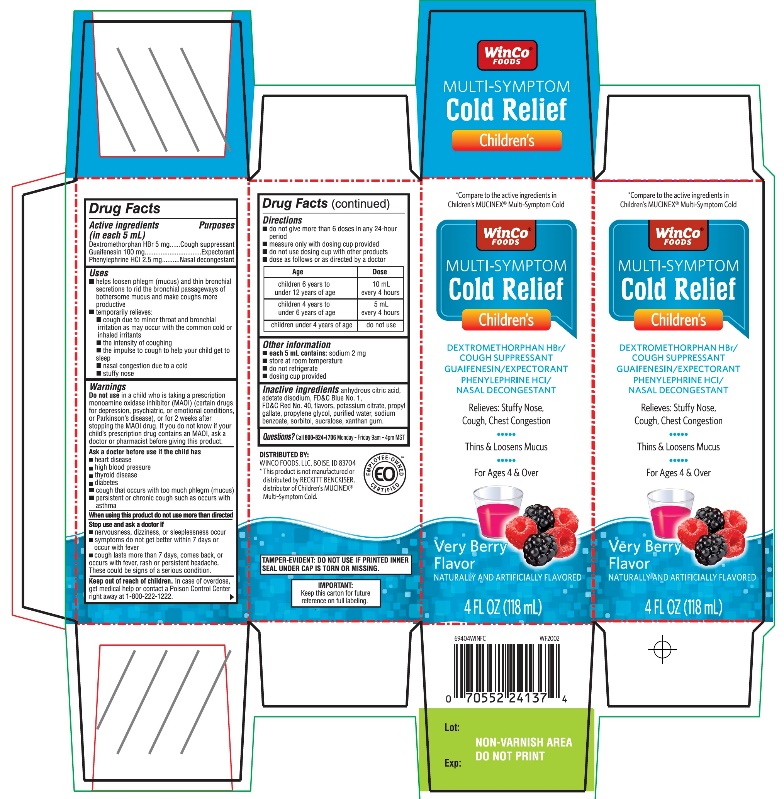 DRUG LABEL: Winco Foods Childrens Multi Symptom Cold
NDC: 67091-355 | Form: SUSPENSION
Manufacturer: WINCO FOODS, LLC
Category: otc | Type: HUMAN OTC DRUG LABEL
Date: 20251202

ACTIVE INGREDIENTS: DEXTROMETHORPHAN HYDROBROMIDE 5 mg/5 mL; GUAIFENESIN 100 mg/5 mL; PHENYLEPHRINE HYDROCHLORIDE 2.5 mg/5 mL
INACTIVE INGREDIENTS: ANHYDROUS CITRIC ACID; EDETATE DISODIUM; FD&C RED NO. 40; POTASSIUM CITRATE; PROPYL GALLATE; PROPYLENE GLYCOL; WATER; SODIUM BENZOATE; SORBITOL; SUCRALOSE; XANTHAN GUM

Winco Mucinex® Children's Multi-Symptom Cold

Drug Facts

ACTIVE INGREDIENT

PURPOSE

Active ingredients (in each 5 mL) | Purposes
Dextromethorphan HBr 5 mg | Cough suppressant
Guaifenesin 100 mg | Expectorant
Phenylephrine HCl 2.5 mg | Nasal decongestant

Uses

- helps loosen phlegm (mucus) and thin bronchial secretions to rid the bronchial passageways of bothersome mucus and make coughs more productive
- temporarily relieves:
  - cough due to minor throat and bronchial irritation as may occur with the common cold or inhaled irritants
  - the intensity of coughing
  - the impulse to cough to help your child get to sleep
  - nasal congestion due to a cold
  - stuffy nose

Warnings

DO NOT USE

Do not usein a child who is taking a prescription monoamine oxidase inhibitor (MAOI) (certain drugs for depression, psychiatric, or emotional conditions, or Parkinson's disease), or for 2 weeks after stopping the MAOI drug. If you do not know if your child's prescription drug contains an MAOI, ask a doctor or pharmacist before giving this product.

Ask a doctor before use if the child has

- heart disease
- high blood pressure
- thyroid disease
- diabetes
- cough that occurs with too much phlegm (mucus)
- persistent or chronic cough such as occurs with asthma

When using this product do not use more than directed

Stop use and ask a doctor if

- nervousness, dizziness, or sleeplessness occur
- symptoms do not get better within 7 days or occur with fever
- cough lasts more than 7 days, comes back, or occurs with fever, rash, or persistent headache. These could be signs of a serious condition.

Keep out of reach of children.In case of overdose, get medical help or contact a Poison Control Center right away at 1-800-222-1222.

Directions

- do not give more than 6 doses in any 24-hour period
- measure only with dosing cup provided
- do not use dosing cup with other products
- dose as follows or as directed by a doctor

Age | Dose
children 6 years to under 12 years of age | 10 mL every 4 hours
children 4 to under 6 years of age | 5 mL every 4 hours
children under 4 years of age | do not use

Other information

- each 5 mL contains:sodium 2 mg
- store at room temperature
- do not refrigerate
- use dosing cup provided

Inactive ingredients

anhydrous citric acid, edetate disodium, FD&C Blue No. 1, FD&C Red No. 40, flavors, potassium citrate, propyl gallate, propylene glycol, purified water, sodium benzoate, sorbitol, sucralose, xanthan gum

Questions or comments?

1-866-467-2748

PRINCIPAL DISPLAY PANEL - 118 mL Bottle Carton

NDC 67091-355-18
Children's

Multi-Symptom
Cold

Dextromethorphan HBr-Cough Suppressant
Guaifenesin- Expectorant
Phenylephrine HCl - Nasal Decongestant

- Relieves Stuffy Nose
- Controls Cough
- Relieves Chest Congestion
- Breaks up Mucus

Dosing Cup Included

For Ages 4 & Over

Berry Flavor

Naturally and Artificially Flavored

4 FL OZ (118 mL)

IMPORTANT:Keep this carton for future reference on full labeling.

TAMPER-EVEDENT:DO NOT USE IF PRINTED INNER SEAL UNDER CAP IS TORN OR MISSING.

Distributed by:

*This product is not manufactured or distributed by Reckitt Benckiser, distributor of Children’s Mucinex® Multi-Symptom Cold.